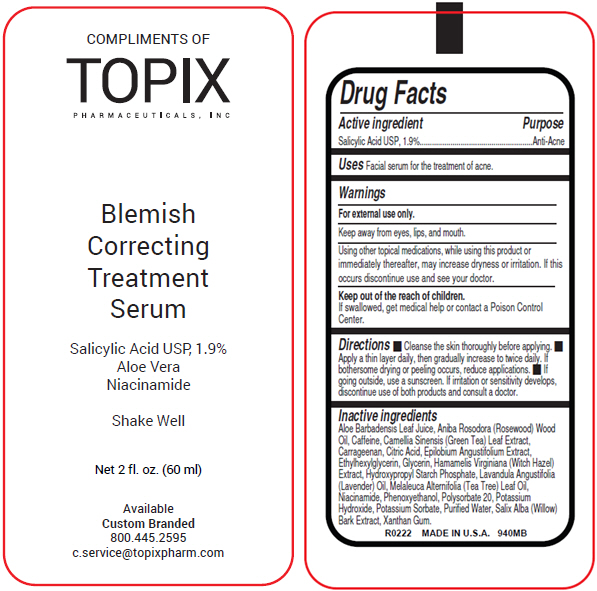 DRUG LABEL: Blemish Correcting
NDC: 51326-940 | Form: LIQUID
Manufacturer: Topiderm, Inc.
Category: otc | Type: HUMAN OTC DRUG LABEL
Date: 20250617

ACTIVE INGREDIENTS: SALICYLIC ACID 109 mg/1 mL
INACTIVE INGREDIENTS: ALOE VERA LEAF; ROSEWOOD OIL; CAFFEINE; GREEN TEA LEAF; CARRAGEENAN; CITRIC ACID MONOHYDRATE; EPILOBIUM ANGUSTIFOLIUM LEAF; ETHYLHEXYLGLYCERIN; GLYCERIN; HAMAMELIS VIRGINIANA TOP; LAVENDER OIL; TEA TREE OIL; NIACINAMIDE; PHENOXYETHANOL; POLYSORBATE 20; POTASSIUM HYDROXIDE; POTASSIUM SORBATE; WATER; SALIX ALBA BARK; XANTHAN GUM

Blemish Correcting
Serum

Drug Facts

Active ingredient

Salicylic Acid USP, 1.9%

Purpose

Anti-Acne

Uses

Facial serum for the treatment of acne.

Warnings

For external use only.

Keep away from eyes, lips, and mouth.

WHEN USING

Using other topical medications, while using this product or immediately thereafter, may increase dryness or irritation. If this occurs discontinue use and see your doctor.

Keep out of the reach of children.

If swallowed, get medical help or contact a Poison Control Center.

Directions

- Cleanse the skin thoroughly before applying.
- Apply a thin layer daily, then gradually increase to twice daily. If bothersome drying or peeling occurs, reduce applications.
- If going outside, use a sunscreen. If irritation or sensitivity develops, discontinue use of both products and consult a doctor.

Inactive ingredients

Aloe Barbadensis Leaf Juice, Aniba Rosodora (Rosewood) Wood Oil, Caffeine, Camellia Sinensis (Green Tea) Leaf Extract, Carrageenan, Citric Acid, Epilobium Angustifolium Extract, Ethylhexylglycerin, Glycerin, Hamamelis Virginiana (Witch Hazel) Extract, Hydroxypropyl Starch Phosphate, Lavandula Angustifolia (Lavender) Oil, Melaleuca Alternifolia (Tea Tree) Leaf Oil, Niacinamide, Phenoxyethanol, Polysorbate 20, Potassium Hydroxide, Potassium Sorbate, Purified Water, Salix Alba (Willow) Bark Extract, Xanthan Gum.

PRINCIPAL DISPLAY PANEL - 60 ml Jar Label

COMPLIMENTS OF
TOPIX
PHARMACEUTICALS, INC

Blemish
Correcting
Treatment
Serum

Salicylic Acid USP, 1.9%
Aloe Vera
Niacinamide

Shake Well

Net 2 fl. oz. (60 ml)

Available
Custom Branded
800.445.2595
c.service@topixpharm.com